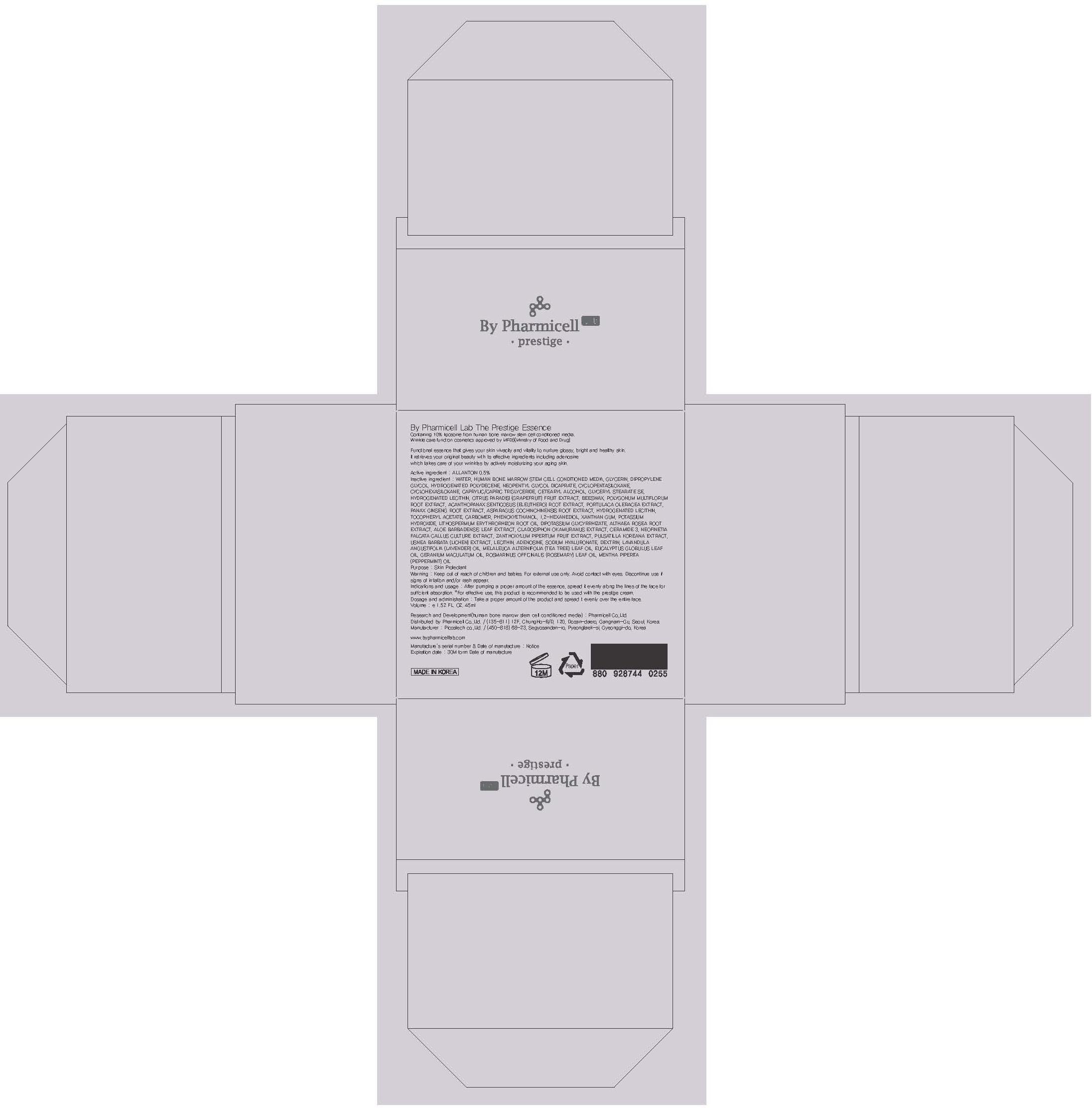 DRUG LABEL: By Pharmicell Lab The Prestige Essence
NDC: 60949-020 | Form: CREAM
Manufacturer: Pharmicell Co., Ltd.
Category: otc | Type: HUMAN OTC DRUG LABEL
Date: 20131119

ACTIVE INGREDIENTS: ALLANTOIN 0.22 mg/45 mL
INACTIVE INGREDIENTS: WATER; GLYCERIN

ACTIVE INGREDIENT

Active ingredient : ALLANTOIN 0.5%

INACTIVE INGREDIENT

Inactive ingredient : WATER, HUMAN BONE MARROW STEM CELL CONDITIONED MEDIA, GLYCERIN, DIPROPYLENE GLYCOL, HYDROGENATED POLYDECENE, NEOPENTYL GLYCOL DICAPRATE, CYCLOPENTASILOXANE, CYCLOHEXASILOXANE, CAPRYLIC/CAPRIC TRIGLYCERIDE, CETEARYL ALCOHOL, GLYCERYL STEARATE SE, HYDROGENATED LECITHIN, CITRUS PARADISI (GRAPEFRUIT) FRUIT EXTRACT, BEESWAX, POLYGONUM MULTIFLORUM ROOT EXTRACT, ACANTHOPANAX SENTICOSUS (ELEUTHERO) ROOT EXTRACT, PORTULACA OLERACEA EXTRACT, PANAX GINSENG ROOT EXTRACT, ASPARAGUS COCHINCHINENSIS ROOT EXTRACT, HYDROGENATED LECITHIN, TOCOPHERYL ACETATE, CARBOMER, PHENOXYETHANOL, 1,2-HEXANEDIOL, XANTHAN GUM, POTASSIUM HYDROXIDE, LITHOSPERMUM ERYTHRORHIZON ROOT OIL, DIPOTASSIUM GLYCYRRHIZATE, ALTHAEA ROSEA ROOT EXTRACT, ALOE BARBADENSIS LEAF EXTRACT, CLADOSIPHON OKAMURANUS EXTRACT, CERAMIDE 3, NEOFINETIA FALCATA CALLUS CULTURE EXTRACT, ZANTHOXYLUM PIPERITUM FRUIT EXTRACT, PULSATILLA KOREANA EXTRACT, USNEA BARBATA (LICHEN) EXTRACT, LECITHIN, ADENOSINE, SODIUM HYALURONATE, DEXTRIN, LAVANDULA ANGUSTIFOLIA (LAVENDER) OIL, MELALEUCA ALTERNIFOLIA (TEA TREE) LEAF OIL, EUCALYPTUS GLOBULUS LEAF OIL, GERANIUM MACULATUM OIL, ROSMARINUS OFFICINALIS (ROSEMARY) LEAF OIL, MENTHA PIPERITA (PEPPERMINT) OIL

PURPOSE

Purpose : Skin Protectant

WARNINGS

Warning : Keep out of reach of children and babies. For external use only. Avoid contact with eyes. Discontinue use if signs of irritation and/or rash appear.

Keep out of reach of children and babies

Indications and usage : After pumping a proper amount of the essence, spread it evenly along the lines of the face for sufficient absorption.

Dosage and administration : Take a proper amount of the product and spread it evenly over the entire face.